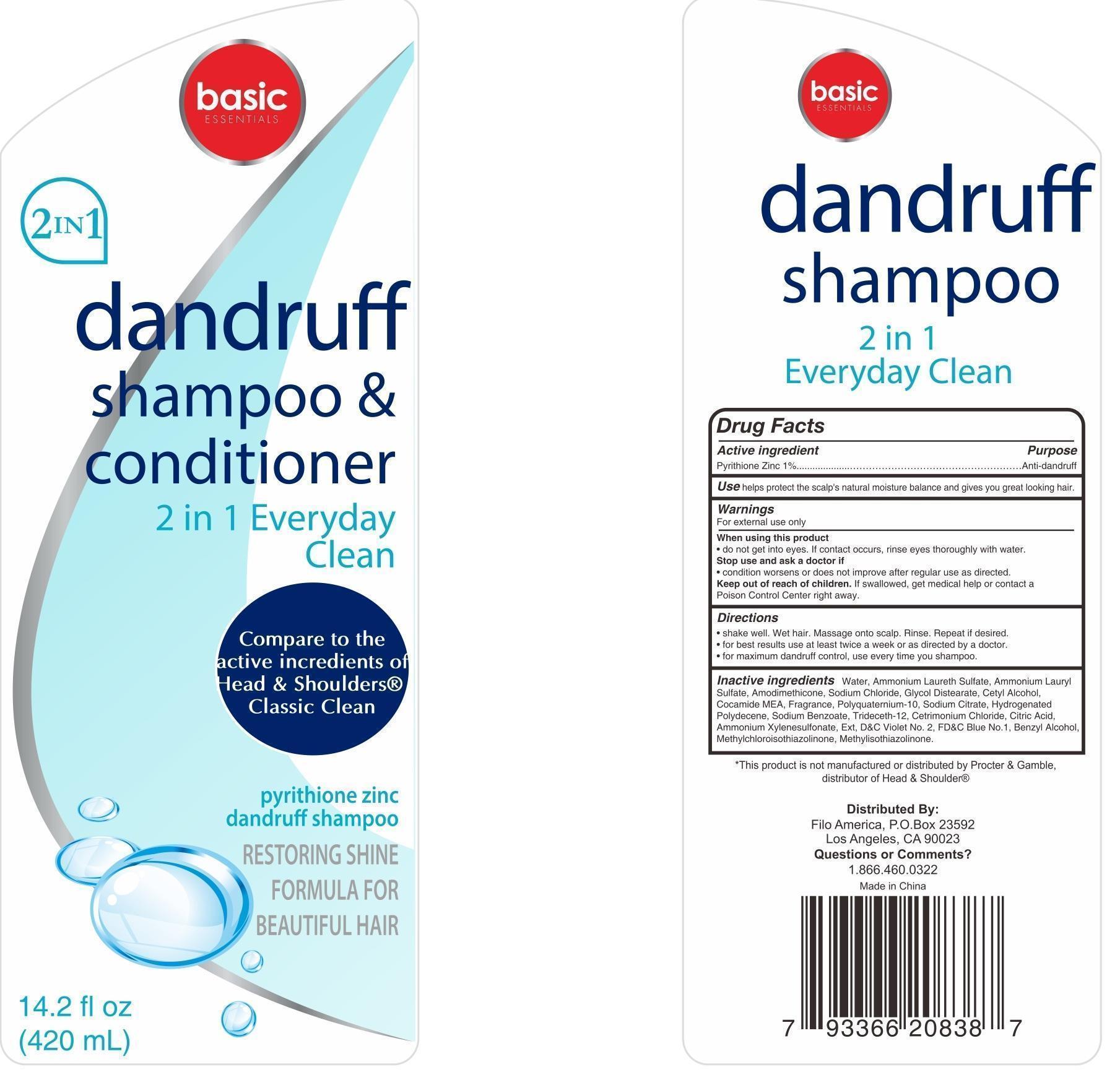 DRUG LABEL: basic essentials dandruff (clean and conditioner)
NDC: 50438-606 | Form: SHAMPOO
Manufacturer: Filo America
Category: otc | Type: HUMAN OTC DRUG LABEL
Date: 20150610

ACTIVE INGREDIENTS: PYRITHIONE ZINC 1 g/100 mL
INACTIVE INGREDIENTS: water; cocamidopropyl betaine; glycol stearate; CARBOMER COPOLYMER TYPE A; ammonium chloride; methylchloroisothiazolinone; methylisothiazolinone; CITRIC ACID MONOHYDRATE; EDETATE DISODIUM; FD&C BLUE NO. 1; FD&C RED NO. 4; ZINC CARBONATE; BENZYL ALCOHOL; GUAR HYDROXYPROPYLTRIMONIUM CHLORIDE (1.7 SUBSTITUENTS PER SACCHARIDE); SODIUM XYLENESULFONATE; MAGNESIUM CARBONATE HYDROXIDE; SODIUM LAURYL SULFATE

Drug Facts

Active Ingredient Purpose

Zinc Pyrithione 1% Anti-dandruff

PURPOSE

Helps prevent recurrence of flaking and itching associated with dandruff.

KEEP OUT OF REACH OF CHILDREN

If swallowed, get medical help or contact a Poison Control Center right away.

Do not get into eyes, if contact occurs, rinse eyes thoroughly with water.

INDICATIONS AND USAGE

Shake well, wet hair, massage onto scalp. Rinse, repeat if desired.

For best results, use at least twice a week or as directed by a doctor.

For maximum dandruff control, use every time you shampoo.

WARNINGS

For external use only.

Stop use and ask a doctor if Condition worsens or does not improve after regular use as directed.

DOSAGE AND ADMINISTRATION

apply as needed.

INACTIVE INGREDIENT

water, sodium laureth sulfate, cocamidopropyl betaine, sodium lauroamphoacetate, glycol stearate, acrylates/acrylamide copolymer, ammonium chloride, methylchloroisothiazolinone, methylisothiazolinone, fragrance, citric acid, guar hydroxypropyltrimonium chloride, titanium dioxide, disodium EDTA, zinc chloride, blue 1, red 4